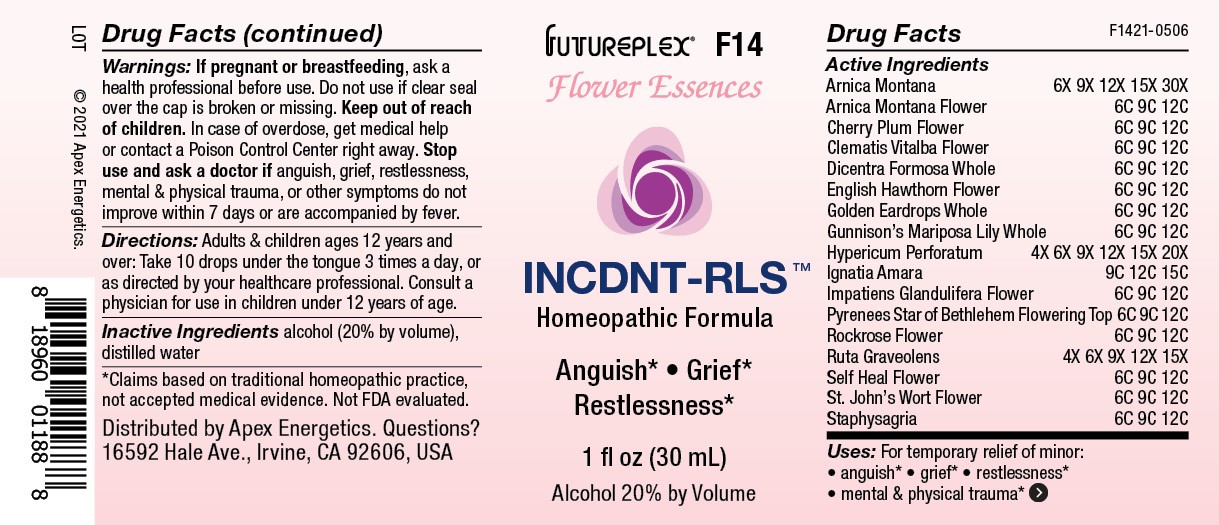 DRUG LABEL: F14
NDC: 63479-0614 | Form: SOLUTION/ DROPS
Manufacturer: Apex Energetics Inc.
Category: homeopathic | Type: HUMAN OTC DRUG LABEL
Date: 20240108

ACTIVE INGREDIENTS: CLEMATIS VITALBA FLOWER 12 [hp_C]/1 mL; DICENTRA FORMOSA WHOLE 12 [hp_C]/1 mL; CRATAEGUS MONOGYNA FLOWER 12 [hp_C]/1 mL; EHRENDORFERIA CHRYSANTHA WHOLE 12 [hp_C]/1 mL; HELIANTHEMUM NUMMULARIUM FLOWER 12 [hp_C]/1 mL; RUTA GRAVEOLENS FLOWERING TOP 15 [hp_X]/1 mL; ARNICA MONTANA 30 [hp_X]/1 mL; ARNICA MONTANA FLOWER 12 [hp_C]/1 mL; PRUNUS CERASIFERA FLOWER 12 [hp_C]/1 mL; HYPERICUM PERFORATUM FLOWER 12 [hp_C]/1 mL; HYPERICUM PERFORATUM 20 [hp_X]/1 mL; PRUNELLA VULGARIS FLOWER 12 [hp_C]/1 mL; CALOCHORTUS GUNNISONII WHOLE 12 [hp_C]/1 mL; STRYCHNOS IGNATII SEED 15 [hp_C]/1 mL; IMPATIENS GLANDULIFERA FLOWER 12 [hp_C]/1 mL; ORNITHOGALUM UMBELLATUM FLOWERING TOP 12 [hp_C]/1 mL; DELPHINIUM STAPHISAGRIA SEED 12 [hp_C]/1 mL
INACTIVE INGREDIENTS: WATER; ALCOHOL

F14

Active Ingredients
Arnica Montana | 6X 9X 12X 15X 30X
Arnica Montana Flower | 6C 9C 12C
Cherry Plum Flower | 6C 9C 12C
Clematis Vitalba Flower | 6C 9C 12C
Dicentra Formosa Whole | 6C 9C 12C
English Hawthron Flower | 6C 9C 12C
Golden Eardrops Whole | 6C 9C 12C
Gunnison's Mariposa Lily Whole | 6C 9C 12C
Hypericum Perforatum | 4X 6X 9X 12X 15X 20X
Ignatia Amara | 9C 12C 15C
Impatiens Glandulifera Flower | 6C 9C 12C
Pyrenees Star Of Bethlehem Flowering Top | 6C 9C 12C
Rockrose Flower | 6C 9C 12C
Ruta Graveolens | 4X 6X 9X 12X 15X
Self Heal Flower | 6C 9C 12C
St. John's Wort Flower | 6C 9C 12C
Staphysagria | 6C 9C 12C

INDICATIONS AND USAGE

Uses:

For temporary relief of minor:

• anguish*

• grief*

• restlessness*
• mental & physical trauma*

*Claims based on traditional homeopathic practice, not accepted medical evidence. Not FDA evaluated.

Warnings:

PREGNANCY OR BREAST FEEDING

If pregnant or breastfeeding, ask a health professional before use.

Do not use if clear seal over the cap is broken or missing.

Keep out of reach of children. In case of overdose, get medical help or contact a Poison Control Center right away.

Stop use and ask a doctor if anguish, grief, restlessness,mental & physical trauma, or other other symptoms do not improve within 7 days or are accompanied by fever.

Directions:

Adults & children ages 12 years and over: Take 10 drops under the tongue 3 times a day, or as directed by your healthcare professional. Consult a physician for use in children under 12 years of age.

Inactive Ingredients

alcohol (20% by volume), distilled water

Distributed by Apex Energetics. Questions?

16592 Hale Ave., Irvine, CA 92606, USA

PACKAGE LABEL

FUTUREPLEX® F14

Flower Essences

INCDNT-RLS™

Homeopathic Formula

Anguish* Grief*
Restlessness*

1 fl oz (30 mL)

Alcohol 20% by Volume